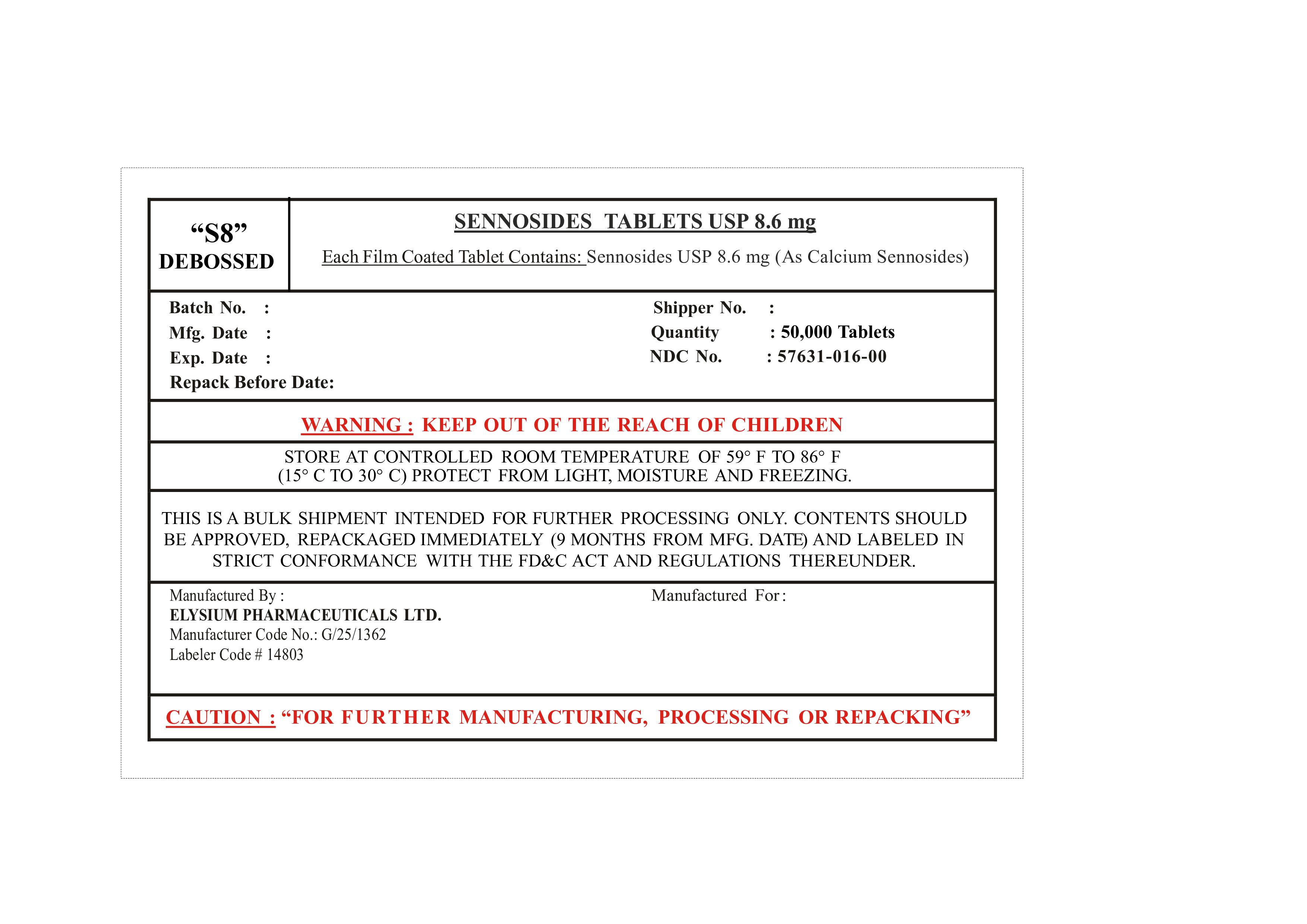 DRUG LABEL: Sennosides
NDC: 57631-016 | Form: TABLET
Manufacturer: InvaTech Pharma Solutions LLC
Category: otc | Type: HUMAN OTC DRUG LABEL
Date: 20251003

ACTIVE INGREDIENTS: SENNA ALATA LEAF 8.6 mg/1 1
INACTIVE INGREDIENTS: PARAFFINUM LIQUIDUM; MAGNESIUM STEARATE; DICALCIUM PHOSPHATE; SODIUM LAURYL SULFATE; HYPROMELLOSES; MICROCRYSTALLINE CELLULOSE; CROSCARMELLOSE SODIUM; SILICON DIOXIDE

Sennosides Tablets USP 8.6 mg

PURPOSE

FOR FURTHER MANUFACTURING, PROCESSING OR REPACKING

KEEP OUT OF THE REACH OF CHILDREN

INDICATIONS AND USAGE

Laxative

DOSAGE AND ADMINISTRATION

FOR MANUFACTURING, PROCESSING OR REPACKING

WARNINGS

KEEP OUT OF THE REACH OF CHILDREN

INACTIVE INGREDIENT

Microcrystalline Cellulose, Dicalcium Phosphate, Croscarmellose Sodium, Stearic acid Powder, Colloidal Silicon Dioxide, Magnesium Stearate, Hypromellose, Polyethylene glycol, , Titanium dioxide, FD&C red